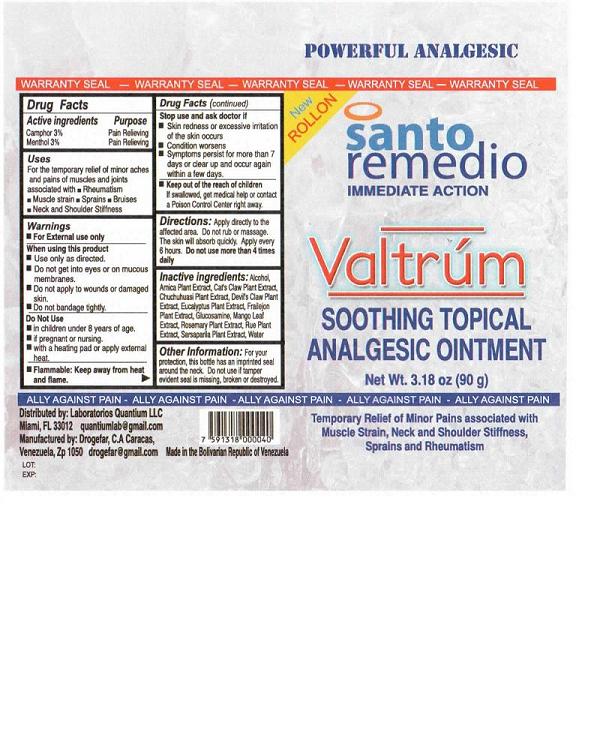 DRUG LABEL: Valtrum Soothing Topical Analgesic
NDC: 50786-003 | Form: OINTMENT
Manufacturer: Drogefar C.A.
Category: otc | Type: HUMAN OTC DRUG LABEL
Date: 20100512

ACTIVE INGREDIENTS: CAMPHOR (SYNTHETIC) 3 mg/100 mg; MENTHOL 3 mg/100 mg
INACTIVE INGREDIENTS: ALCOHOL; ARNICA MONTANA; CAT'S CLAW; GLUCOSAMINE; WATER

VALTRUM Soothing Topical Analgesic Ointment

DRUG FACTS:

Active Ingredients Purpose

Camphor 3% Pain Relieving

Menthol 3% Pain Relieving

USES

For the temporary relief of minor aches and pains of muscles and joints associated with

rheumatism

muscle strain

sprains, bruises

neck and shoulder stiffness

WARNINGS

For external use only

When using this product

Use only as directed

Do not get into eyes or on mucous membranes

Do not apply to wounds or damaged skin

Do not bandage tightly.

Do not use

in children under 8 years of age

if pregnant or nursing

with a heating pad or apply external heat

Flammable: Keep away from heat and flame

Stop use and ask doctor if:

Skin redness or excessive irritation of the skin occurs

Condition worsens

Symptoms persist for more than 7 days or clear up and occur again within a few days

Keep out of reach of children

If swallowed, get medical help or contact a Poison Control Center right away.

Directions:

Apply directly to the affected area. Do not rub or massage. The skin will absorb quickly. Apply every 6 hours. Do not use more than 4 times daily.

Inactive Ingredients:

Alcohol, Arnica Plant Extract, Cat's Claw Plant Extract, Chuchuhuasi Plant Extract, Devil's Claw Plant Extract, Eucalyptus Plant Extract, Frailejon Plant Extract, Glucosamine, Mango Leaf Extract, Rosemary Plant Extract, Rue Plant Extract, Sarsaparila Plant Extract, Water

Other Information:

For your protection, this bottle has an imprinted seal around the neck. Do not use if tamper evident seal is missing, broken or destroyed.

PACKAGE LABEL

POWERFUL ANALGESIC

WARRANTY SEAL - WARRANTY SEAL - WARRANTY SEAL - WARRANTY SEAL - WARRANTY SEAL

New ROLLON

santo remedio

IMMEDIATE ACTION

VALTRUM

Soothing Topical Analgesic Ointment

Net Wt. 3.18oz (90g)

ALLY AGAINST PAIN - ALLY AGAINST PAIN - ALLY AGAINST PAIN - ALLY AGAINST PAIN - ALLY AGAINST PAIN -

Distributed by Laboratorios Quantium LLC

Miami, FL 33012 quantiumlab@gmail.com

Manufactured by: Drogefar, C.A. Caracas,

Venezuela, Zp 1050

Lot:

Exp:

Made In the Bolivian Republic of Venezuela

Temporary relief of minor pains associated with Muscle Strain, Neck and Shoulder Stiffness, Sprains and Rheumatism